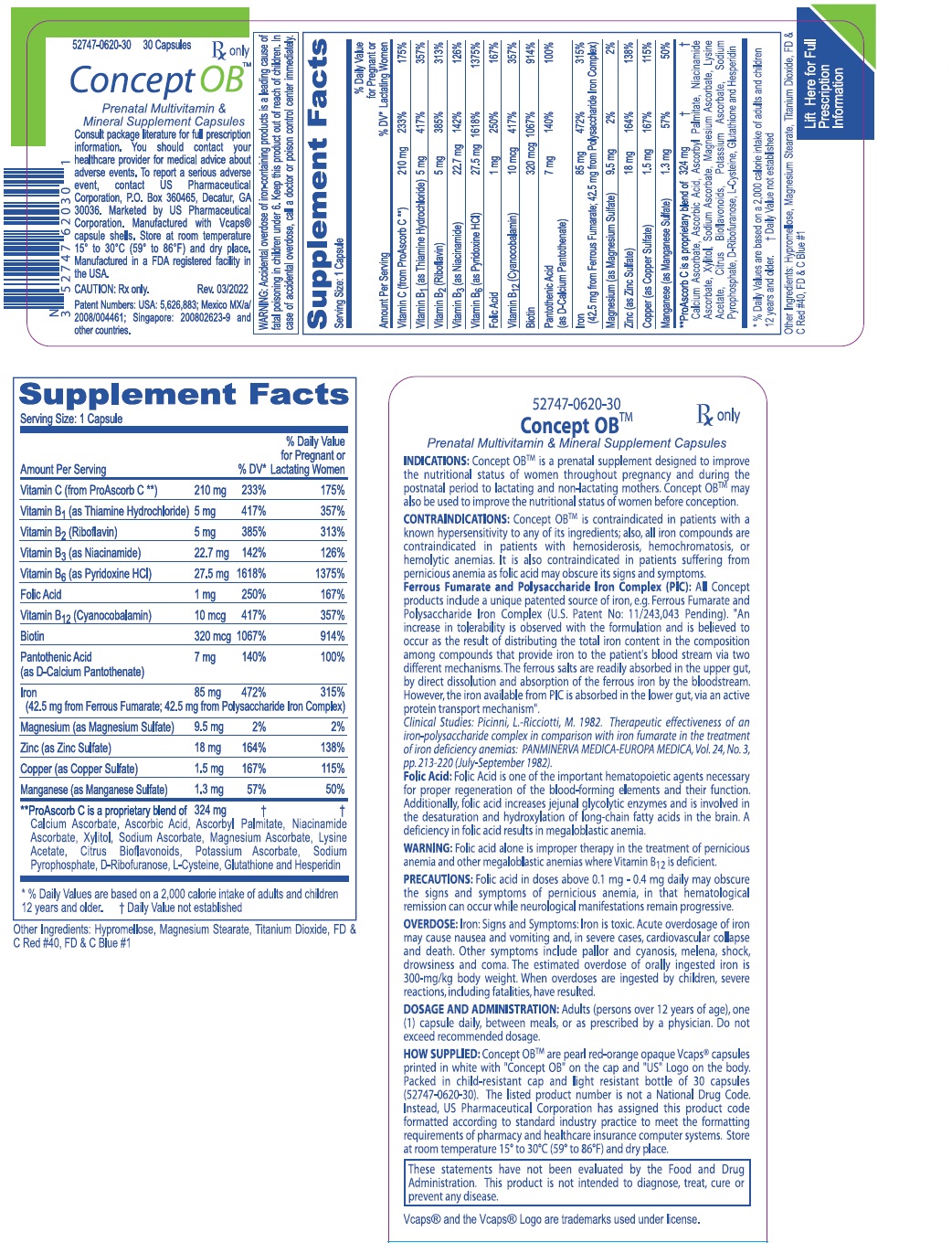 DRUG LABEL: Concept OB 
NDC: 52747-620 | Form: CAPSULE
Manufacturer: U.S. Pharmaceutical Corporation
Category: prescription | Type: HUMAN PRESCRIPTION DRUG LABEL
Date: 20221108

ACTIVE INGREDIENTS: FERROUS FUMARATE 42.5 mg/1 1; IRON  42.5 mg/1 1; ASCORBIC ACID 210 mg/1 1; FOLIC ACID 1 mg/1 1; THIAMINE MONONITRATE 5 mg/1 1; RIBOFLAVIN 5 mg/1 1; NIACIN 20 mg/1 1; CALCIUM PANTOTHENATE 7 mg/1 1; PYRIDOXINE HYDROCHLORIDE 25 mg/1 1; BIOTIN 300 ug/1 1; CYANOCOBALAMIN 10 ug/1 1; CUPRIC SULFATE  800 ug/1 1; MAGNESIUM SULFATE, UNSPECIFIED FORM 6.9 mg/1 1; MANGANESE SULFATE 1.3 mg/1 1; ZINC SULFATE, UNSPECIFIED FORM 18.2 mg/1 1
INACTIVE INGREDIENTS: HYPROMELLOSE, UNSPECIFIED; MAGNESIUM STEARATE; TITANIUM DIOXIDE; FD&C RED NO. 40; FD&C BLUE NO. 1

see all prescribing information for Concept OB

DESCRIPTION

DESCRIPTION: Each capsule contains: Ferrous Fumarate (anhydrous) .....................................130 mg (Equivalent to about 42.5 mg of Elemental Iron) PolysaccharideIronComplex .....................................92.4mg (Equivalent to about 42.5 mg of Elemental Iron) Vitamin C (from ProAscorb C‡)..................................... 210 mg Folic Acid ................................................................................... 1 mg Thiamine Mononitrate (B1)................................................. 5 mg Riboflavin (B2).......................................................................... 5 mg Niacin (B3)...............................................................................20 mg d-Calcium Pantothenate (B5)............................................. 7 mg Pyridoxine HCl (B6) ..............................................................25 mg Biotin (B7)........................................................................... 300 mcg Cyanocobalamin (B12) .....................................................10 mcg Copper (as Copper Sulfate)..........................................800 mcg Magnesium (as Magnesium Sulfate)............................6.9 mg Manganese (as Manganese Sulfate).............................1.3 mg Zinc (as Zinc Sulfate) ....................................................... 18.2 mg Inactive Ingredients: Hypromellose, Silicon Dioxide, Magnesium Stearate, Carmine, and Candurin Silver Fine.

CLINICAL PHARMACOLOGY

CLINICAL PHARMACOLOGY: Concept OBTM also supplies important prenatal vitamin minerals in a formulation that was especially designed to supplement the nutritional needs of pregnant women, before, during and after pregnancy. In Concept OBTM, patients receive the balanced support of 14 essential vitamins and minerals, including 1 mg of folic acid. The essential role of iron supplementation for pregnant women has long been recognized. Concept OBTM is unique in that it utilizes two (2) different forms of iron, i.e., Ferrous Fumarate and Polysaccharide Iron Complex (as cell-contracted akaganèite), making available a total of 85 mg of elemental iron per capsule as follows:
Ferrous Fumarate (anhydrous) 130 mg Polysaccharide iron complex (PIC) 92.4 mg
Ferrous Fumarate: Provides about 42.5 mg of elemental iron per dose. Ferrous Fumarate is an anhydrous salt of a combination of ferrous iron and fumaric acid, containing 33% of iron per weight. The acute toxicity in experimental animals is low and Ferrous Fumarate is well tolerated clinically. As a ferrous salt, it is more efficiently absorbed in the duodenum. Ferrous Fumarate contrasts very favorably with the availability of the 20% of elemental iron of ferrous sulfate, and the 13% of elemental iron of ferrous gluconate.
Polysaccharide Iron Complex: Provides about 42.5 mg elemental iron, as a cell-contracted akaganèite. It is a product of ferric iron complexed to a low molecular weight polysaccharide. This polysaccharide is produced by the extensive hydrolysis of starch and is a dark brown powder that dissolves in water to form a very dark brown solution, which is virtually odorless and tasteless.
The most frequent cause of anemia in pregnant women is iron deficiency. Because of the continuous loss of iron due to monthly menstruation, most women enter pregnancy with less than optimal iron stores. Supplementation of iron must suffice to meet the needs for maternal and fetal erythropoisis, and account for daily maternal gastrointestinal losses and obligate fetal transfer and growth. Iron requirements during pregnancy usually cannot be met with the average diet. (ACOG technical bulletin (1993): Nutrition during Pregnancy. p.4. Number 179-April 1993: The American College of Obstetricians and Gynecologists, Washington, D.C. 20024-2188).
Concept OBTM does not contain calcium, as calcium may inhibit iron absorption because of the binding or conversion of ferrous salts by calcium and other minerals. Calcium salts can always be prescribed separately for women at high nutritional risk, including those who do not eat adequate amounts of dairy products. The recommendation of the National Academy of Sciences Tenth Ed. 1989 National Academy Press, Washington, D.C., suggests the supplementation of 1200 mg of calcium for pregnant and lactating women for the prevention of calcium deficiency.
Folic acid is a hematopoetic vitamin and has been used extensively for the prevention of neural tube defects. The need for folic acid in pregnancy, with its increased demands of the fetus, or lactation, is not being met by normal dietary sources. Concept OBTM capsules contain 1 mg of folic acid. Neural tube defects (NTD's) are the most common birth defects that result in infant mortality and serious disability. For women with a previous pregnancy that resulted in a child with a neural tube malformation, the use of 4 mg/d of folic acid has been reported to be effective in preventing a recurrence (MRC Vitamin Study Research Group, 1991). However, earlier studies from the United Kingdom suggested that lower daily doses, for example 0.36 mg, might result in a comparable reduction of a recurrence of NTD's. Since neural tube closure is complete by four weeks following conception, beginning folic acid supplementation after that time is not likely to be of any value. It should be noted that a daily 4 mg dose of folic acid did not prevent all NTD's in the MRC study. Patients should be cautioned that folic acid supplementation does not preclude the need for consideration for prenatal testing for NTD's (ACOG Committee Opinion, Number 120, March 1993: The American College of Obstetricians and Gynecologists, Washington D.C. 20024-2188). The U.S. Public Health Service has recommended that all women of childbearing age in the United States who are capable of becoming pregnant should consume 0.4 mg of folic acid per day for reducing their risk of having a pregnancy affected with spina bifida or other NTD's (Center of Disease Control, 1992). Recommendation for the use of folic acid to reduce the number of cases of spina bifida and other neural tube defects: MMWR 1992: 41(RR14): 1-7). Concept OBTM has been formulated without the addition of vitamins A, D, E and K. These fat-soluble vitamins can accumulate and lead to birth defects. Supplementation of vitamins A, D, E and K should be based on an individual need assessment.
All ConceptTM products include a unique patented source of iron, e.g. Ferrous Fumarate and Polysaccharide Iron Complex (U.S. Patent No: 11/243,043 Pending). An increase in tolerability is observed with the (patented formulation) and is believed to occur as the result of distributing the total iron content in the composition among compounds that
NDC 52747-620-30 Concept OBTM Prescription Prenatal Postnatal Vitamin Mineral Capsules
52747620300709
Back side Concept OB LC-10807 Rev 07/2009
provide iron to the patient's blood stream via two different mechanisms. The ferrous salts are readily absorbed in the upper gut, by direct dissolution and absorption of the ferrous iron by the bloodstream. However, the iron available from PIC is absorbed in the lower gut, via an active protein transport mechanism". The Concept OBTM formulation also supplies additional important prenatal vitamin and minerals, which supplement the nutritional needs of pregnant women, before, during and after pregnancy. Deficiencies of these ingredients are common during pregnancy and lactation.

CLINICAL STUDIES

Clinical Studies: Because Ferrous Fumarate is an organic complex, it contains no free ions, either ferric or ferrous. Polysaccharide Iron Complex is clinically non-toxic. Prior studies in rats demonstrated that Polysaccharide Iron Complex (PIC), administered as a single oral dose to Sprague Dawley rats did not produce evidence of toxicity at a dosage level of 5000 mg Iron/kg: (An Acute Oral Toxicity Study in Rats with Polysaccharide-Iron Complex. T.N.Merriman, M. Aikman and R.E. Rush, Springborn Laboratories. Inc. Spencerville, Ohio Study No. 3340.1 March - April 1994). Other clinical studies had demonstrated that Polysaccharide Iron gives a good hematopoietic response with an almost complete absence of the side effects usually associated with oral iron therapy. Picinni and Ricciotti suggested in 1982, that "the therapeutic effectiveness of Polysaccharide Iron Complex when compared with iron fumarate in the treatment of iron deficiency anemia, appears to be as active as the iron fumarate and as well tolerated, however, it exerted a greater influence on the level of hemoglobin and on the number of red cells..." and that, "it has been exceptionally well tolerated by all patients" (Picinni, L.-Ricciotti, M. 1982. Therapeutic effectiveness of an iron-polysaccharide complex in comparison with iron fumarate in the treatment of iron deficiency anemias): PANMINERVA MEDICA-EUROPA MEDICA, Vol. 24, No. 3, pp. 213-220 (July - September 1982).
As mentioned above, the patented source of iron used in Concept OBTM (Ferrous Fumarate and Polysaccharide Iron Complex) provides a high level of elemental iron with a low incidence of gastric distress.
CONCLUSION: Based on the results of this study, the oral combination of Ferrous Fumarate and Polysaccharide Iron Complex was better tolerated and safer than the oral administration of Ferrous Fumarate alone. The conclusion of this research stated, that the addition of PIC to Ferrous Fumarate surprisingly allows the same concentration of Ferrous Fumarate to be better tolerated than the Ferrous Fumarate alone.

INDICATIONS AND USAGE

INDICATIONS: Concept OBTM is a prenatal supplement designed to improve the nutritional status for women throughout pregnancy and during the postnatal period to lactating and non-lactating mothers. Concept OBTM may also be used to improve the nutritional status of women before conception.

CONTRAINDICATIONS

CONTRAINDICATIONS: Concept OBTM is contraindicated in patients with known hypersensitivity to any of its ingredients; also, all iron compounds are contraindicated in patients with hemosiderosis, hemochromatosis, or hemolytic anemias. Pernicious anemia is a contraindication, as folic acid may obscure its signs and symptoms.

WARNINGS AND PRECAUTIONS

WARNING: Accidental overdose of iron-containing products is a leading cause of fatal poisoning in children under 6. Keep this product out of reach of children. In case of accidental overdose, call a doctor or poison control center immediately. WARNING: Folic acid alone is improper therapy in the treatment for pernicious anemia and other megaloblastic anemias where Vitamin B12 is deficient.
PRECAUTIONS: General: Folic acid in doses above 0.1 mg - 0.4 mg daily may obscure pernicious anemia, in that hematological remission can occur while neurological manifestations remain progressive.

PEDIATRIC USE

Pediatric Use: Safety and effectiveness of this product have not been established in pediatric patients.

GERIATRIC USE

Geriatric Use: No clinical studies have been performed in patients age 65 and over to determine whether older persons respond differently from younger persons. Dosage should always begin at the low end of the dosage scale and should consider that elderly persons may have decreased hepatic, renal, or cardiac function and or concomitant diseases.

ADVERSE REACTIONS

Adverse Reactions: Folic Acid: Allergic sensitizations have been reported following both oral and parenteral administration of folic acid. Ferrous Fumarate: Gastrointestinal disturbances (anorexia, nausea, diarrhea, constipation) occur occasionally, but are usually mild and may subside with continuation of therapy. Although the absorption of iron is best when taken between meals, giving Concept OBTM after meals may control occasional G.I. disturbances. Concept OBTM is best absorbed when taken at bedtime.

OVERDOSAGE

OVERDOSE: Iron: Signs and Symptoms: Iron is toxic. Acute overdosage of iron may cause nausea and vomiting and, in severe cases, cardiovascular collapse and death. Other symptoms include pallor and cyanosis, melena, shock, drowsiness and coma. The estimated overdose of orally ingested iron is 300-mg/kg body weight. When overdoses are ingested by children, severe reactions, including fatalities, have resulted. Concept OBTM should be stored beyond the reach of children to prevent against accidental iron poisoning. Keep this and all other drugs out of the reach of children.
Treatment: For specific therapy, exchange transfusion and chelating agents should be used. For general management, perform gastric lavage with sodium bicarbonate solution or milk. Administer intravenous fluids and electrolytes and use oxygen.

DOSAGE AND ADMINISTRATION: Adults (persons over 12 years of age), One (1) capsule daily, between meals, or as prescribed by a physician. Do not exceed recommended dosage. Do not administer to children under the age of 12.

HOW SUPPLIED

HOW SUPPLIED: Concept OBTM are pearl red-orange opaque Vcaps® capsules printed in white with "Concept OB" on the cap and "US" logo on the body. Packed in child-resistant cap and light resistant bottle of 30 capsules (52747-0620-30). The listed product number is not a National Drug Code. Instead, US Pharmaceutical Corporation has assigned this product code formatted according to standard industry practice to meet the formatting requirements of pharmacy and healthcare insurance computer systems. Store at room temperature 15º to 30ºC (59º to 86ºF) and dry place.

These statements have not been evaluated by the Food and Drug Administration. This product is not intended to diagnose, treat, cure or prevent any disease.

Vcaps® and the Vcaps® Logo are trademarks used under license.